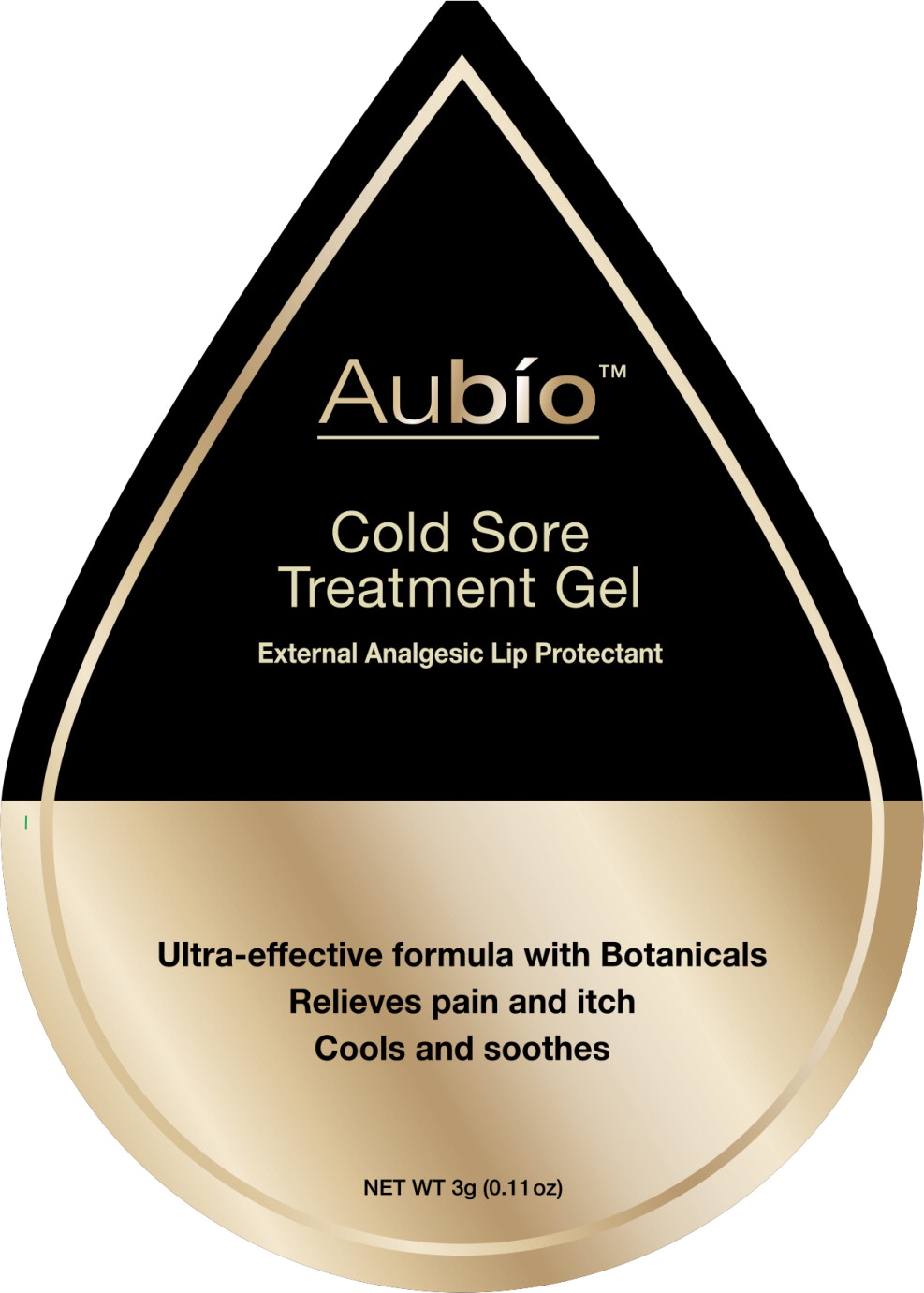 DRUG LABEL: Aubio Life Sciences Lip
NDC: 70365-001 | Form: CREAM
Manufacturer: Aubio Life Sciences LLC
Category: otc | Type: HUMAN OTC DRUG LABEL
Date: 20160131

ACTIVE INGREDIENTS: Allantoin 5 mg/1 g; Lidocaine 5 mg/1 g
INACTIVE INGREDIENTS: Water; Glycerin; Aloe vera Leaf; Carbomer Interpolymer Type A (allyl sucrose crosslinked); Phenoxyethanol; Caprylic Alcohol; Ethylhexylglycerin; Hexylene Glycol; Glycyrrhizinate Dipotassium; Phytosphingosine; Sodium Lauroyl Lactylate; Xanthan Gum; Cholesterol; Ceramide NP; 3-Dehydroxy Ceramide 1; Ceramide AP; Lavandula Angustifolia Flower; Melissa Officinalis; Sarracenia Purpurea

Drug Facts

Active Ingredients

Allantoin 0.50% (W/W)

Lidocaine 0.50% (W/W)

Purpose

skin protectant

external analgesic

Uses

- For the temporary relief of pain and Itching associated with cold sores and fever blisters
- Relieves dryness and softens cold sores and fever blisters

Warnings

For external use only

When using this product

- avoid contact with the eyes

Stop use and ask a doctor

- if condition worsens
- if symptoms persist for more than 7 days or clear up and occur again within a few days.

Keep out of reach of children. If swallowed get medical help or contact a poison control center right away

Questions or comments?

Call Toll-free 1-844-My-Aubío (1-844-692-8246)

Weekdays 9am-5pm PT. If you are not completely satisfied, save receipt and remaining product and call us.

Directions

- Wash hands before and after applying gel
- Gently clean the affected area before applying
- Always rub gently into affected area
- Adults and children 2 years of age and older; apply to affected area not more than 3-4 times daily
- Children under 2 years of age, consult a doctor

Inactive Ingredients

Water (Aqua), Glycerin, Sarracenia Stalk/Flower/Seed Extract (and) Sarracenia Purpurea Leaf/Stalk/ Flower/Seed Extract, Aloe Barbadensis Leaf Juice, Lavandula Angustifolia (Lavender) Flower Extract, Melissa Officinalis (Balm Mint) Extract, Dipotassium Glycyrrhizate, Phytosphingosine, Carbomer, Ceramide AP, Ceramide EOP, Ceramide NP, Cholesterol, Xantham Gum, Sodium Hydroxide, Sodium Lauroyl Lactylate, Hexylene Glycol, Ethylhexylglycerin, Caprylyl Glycol, Phenoxytehanol

Other Information

- Recap after each use
- Store at room temperature
- Protect the product in this container from excessive heat and direct sun

Principal Display Panel - Blister Pack Label

Aubío™

Cold Sore
Treatment Gel

External Analgesic Lip Protectant

Ultra-effective formula with Botanicals

Relieves pain and itch

Cools and soothes

NET WT 3g (0.11 oz)